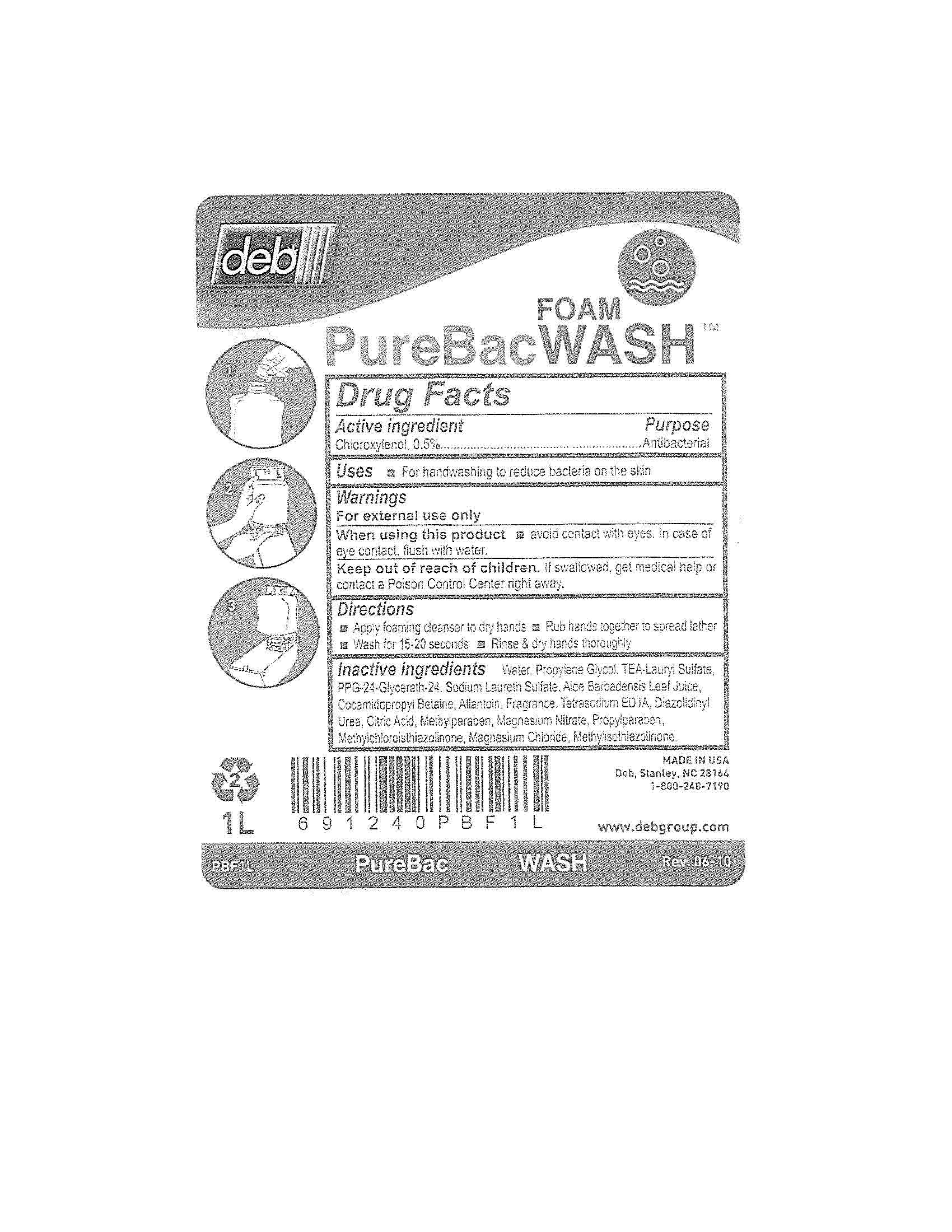 DRUG LABEL: PureBac Foam Wash
NDC: 11084-131 | Form: LIQUID
Manufacturer: Deb USA, Inc.
Category: otc | Type: HUMAN OTC DRUG LABEL
Date: 20100911

ACTIVE INGREDIENTS: CHLOROXYLENOL 0.5 mL/100 mL
INACTIVE INGREDIENTS: WATER; PROPYLENE GLYCOL; TROLAMINE LAURYL SULFATE; SODIUM LAURETH SULFATE; ALOE VERA LEAF; COCAMIDOPROPYL BETAINE; ALLANTOIN; EDETATE SODIUM; DIAZOLIDINYL UREA; CITRIC ACID MONOHYDRATE; METHYLPARABEN; MAGNESIUM NITRATE; PROPYLPARABEN; METHYLCHLOROISOTHIAZOLINONE; MAGNESIUM CHLORIDE; METHYLISOTHIAZOLINONE

Drug Facts

Active ingredient

Chloroxylenol, 0.5%

Purpose

Antibacterial

Uses

For handwashing to reduce bacteria on the skin

Warnings

For external use only

When using this product avoid contact with eyes.

In case of eye contact, flush with water.

Keep out of reach of children.

If swallowed, get medical help or contact a Poison Control Center right away.

Directions

Apply foaming cleanser to dry hands

Rub hands together to spead lather

Wash for 15-20 seconds

Rinse and dry hands thoroughly

Inactive ingredients

Water, Propylene Glycol, TEA-Lauryl Sulfate, PPG-24-Glycereth-24, Sodium Laureth Sulfate, Aloe Barbadensis Leaf Juice, Cocamidopropyl Betaine, Allantoin, Fragrance, Tetrasodium EDTA, Diazolidinyl Urea, Citric Acid, Methylparaben, Magnesium Nitrate, Propylparaben, Methylchloroisothiazolinone, Magnesium Chloride, Methylisothiazolinone.

PACKAGE LABEL

deb

PureBac Foam Wash

MADE IN USA

1L